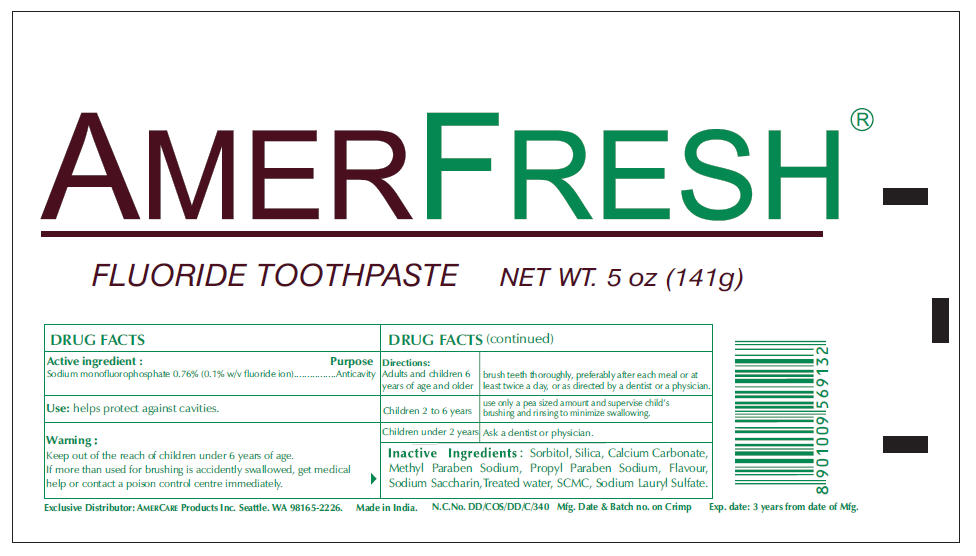 DRUG LABEL: Amerfresh
NDC: 51460-5000 | Form: PASTE, DENTIFRICE
Manufacturer: Amercare Products Inc
Category: otc | Type: HUMAN OTC DRUG LABEL
Date: 20110316

ACTIVE INGREDIENTS: Sodium Monofluorophosphate 0.76 g/100 g
INACTIVE INGREDIENTS: Calcium Carbonate 42 g/100 g; Water; Sorbitol; Silicon Dioxide; Sodium Lauryl Sulfate; Carboxymethylcellulose Sodium; Saccharin Sodium; Methylparaben Sodium; Propylparaben Sodium

AMERFRESH®

FLUORIDE TOOTHPASTE

Active ingredient

Sodium monofluorophosphate 0.76% (0.1% w/v fluoride ion)

Purpose

Anticavity

Use

helps protect against cavities.

Warning

KEEP OUT OF REACH OF CHILDREN

Keep out of the reach of children under 6 years of age.
If more than used for brushing is accidently swallowed, get medical help or contact a poison control centre immediately.

Directions

Adults and children 6 years of age and older | brush teeth thoroughly, preferably after each meal or at least twice a day, or as directed by a dentist or a physician.
Children 2 to 6 years | use only a pea sized amount and supervise child's brushing and rinsing to minimize swallowing.
Children under 2 years | Ask a dentist or physician.

Inactive Ingredients

Sorbitol, Silica, Calcium Carbonate, Methyl Paraben Sodium, Propyl Paraben Sodium, Flavour, Sodium Saccharin,Treated water, SCMC, Sodium Lauryl Sulfate.

Exclusive Distributor: AMERCARE Products Inc. Seattle. WA 98165-2226.

PRINCIPAL DISPLAY PANEL - 141 g Carton Label

AMERFRESH®

FLUORIDE TOOTHPASTE

NET WT. 5 oz (141g)